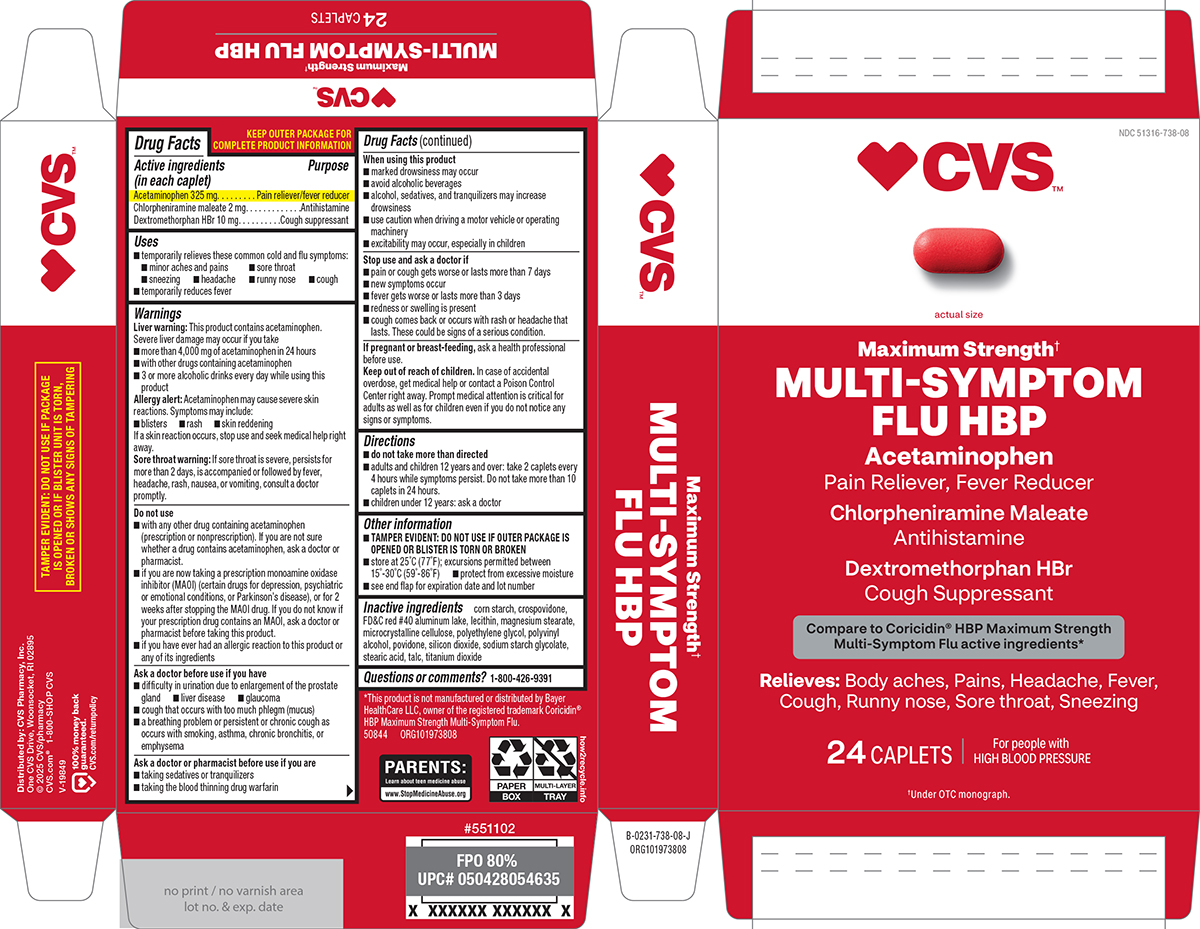 DRUG LABEL: Multi-Symptom Flu HBP
NDC: 51316-738 | Form: TABLET, FILM COATED
Manufacturer: CVS WOONSOCKET PRESCRIPTION CENTER, INCORPORATED
Category: otc | Type: HUMAN OTC DRUG LABEL
Date: 20251117

ACTIVE INGREDIENTS: ACETAMINOPHEN 325 mg/1 1; CHLORPHENIRAMINE MALEATE 2 mg/1 1; DEXTROMETHORPHAN HYDROBROMIDE 10 mg/1 1
INACTIVE INGREDIENTS: STARCH, CORN; CROSPOVIDONE, UNSPECIFIED; FD&C RED NO. 40 ALUMINUM LAKE; LECITHIN, SOYBEAN; MAGNESIUM STEARATE; MICROCRYSTALLINE CELLULOSE; POLYETHYLENE GLYCOL, UNSPECIFIED; POLYVINYL ALCOHOL, UNSPECIFIED; POVIDONE, UNSPECIFIED; SILICON DIOXIDE; SODIUM STARCH GLYCOLATE TYPE A POTATO; STEARIC ACID; TALC; TITANIUM DIOXIDE

CVS 44-738 MS

Active ingredients (in each caplet)

Acetaminophen 325 mg
Chlorpheniramine maleate 2 mg
Dextromethorphan HBr 10 mg

Purpose

Pain reliever/fever reducer
Antihistamine
Cough suppressant

Uses

- temporarily relieves these common cold and flu symptoms:
  - minor aches and pains
  - sore throat
  - sneezing
  - headache
  - runny nose
  - cough
- temporarily reduces fever

Warnings

Liver warning: This product contains acetaminophen. Severe liver damage may occur if you take

- more than 4,000 mg of acetaminophen in 24 hours
- with other drugs containing acetaminophen
- 3 or more alcoholic drinks every day while using this product

Allergy alert: Acetaminophen may cause severe skin reactions. Symptoms may include:

- blisters
- rash
- skin reddening

If a skin reaction occurs, stop use and seek medical help right away.

Sore throat warning: If sore throat is severe, persists for more than 2 days, is accompanied or followed by fever, headache, rash, nausea, or vomiting, consult a doctor promptly.

Do not use

- with any other drug containing acetaminophen (prescription or nonprescription). If you are not sure whether a drug contains acetaminophen, ask a doctor or pharmacist.
- if you are now taking a prescription monoamine oxidase inhibitor (MAOI) (certain drugs for depression, psychiatric or emotional conditions, or Parkinson's disease), or for 2 weeks after stopping the MAOI drug. If you do not know if your prescription drug contains an MAOI, ask a doctor or pharmacist before taking this product.
- if you have ever had an allergic reaction to this product or any of its ingredients

Ask a doctor before use if you have

- difficulty in urination due to enlargement of the prostate gland
- liver disease
- glaucoma
- cough that occurs with too much phlegm (mucus)
- a breathing problem or persistent or chronic cough as occurs with smoking, asthma, chronic bronchitis, or emphysema

Ask a doctor or pharmacist before use if you are

- taking sedatives or tranquilizers
- taking the blood thinning drug warfarin

When using this product

- avoid alcoholic beverages
- marked drowsiness may occur
- alcohol, sedatives, and tranquilizers may increase drowsiness
- excitability may occur, especially in children
- use caution when driving a motor vehicle or operating machinery

Stop use and ask a doctor if

- pain or cough gets worse or lasts more than 7 days
- new symptoms occur
- fever gets worse or lasts more than 3 days
- redness or swelling is present
- cough comes back or occurs with rash or headache that lasts. These could be signs of a serious condition.

If pregnant or breast-feeding,

ask a health professional before use.

Keep out of reach of children.

In case of accidental overdose, get medical help or contact a Poison Control Center right away. Prompt medical attention is critical for adults as well as for children even if you do not notice any signs or symptoms.

Directions

- do not take more than directed
- adults and children 12 years and over: take 2 caplets every 4 hours while symptoms persist. Do not take more than 10 caplets in 24 hours.
- children under 12 years: ask a doctor

Other information

- TAMPER EVIDENT: DO NOT USE IF OUTER PACKAGE IS OPENED OR BLISTER IS TORN OR BROKEN
- store at 25°C (77°F); excursions permitted between 15°-30°C (59°-86°F)
- protect from excessive moisture
- see end flap for expiration date and lot number

Inactive ingredients

corn starch, crospovidone, FD&C red #40 aluminum lake, lecithin, magnesium stearate, microcrystalline cellulose, polyethylene glycol, polyvinyl alcohol, povidone, silicon dioxide, sodium starch glycolate, stearic acid, talc, titanium dioxide

Questions or comments?

1-800-426-9391

Principal Display Panel

♥︎CVS™

NDC 51316-738-08

actual size

Maximum Strength†
MULTI-SYMPTOM
FLU HBP

Acetaminophen
Pain Reliever, Fever Reducer
Chlorpheniramine Maleate
Antihistamine
Dextromethorphan HBr
Cough Suppressant

Compare to Coricidin® HBP Maximum Strength
Multi-Symptom Flu active ingredients*

Relieves: Body aches, Pains, Headache, Fever,
Cough, Runny nose, Sore throat, Sneezing

24 CAPLETS
For people with
HIGH BLOOD PRESSURE

†Under OTC monograph.

TAMPER EVIDENT: DO NOT USE IF PACKAGE
IS OPENED OR IF BLISTER UNIT IS TORN,
BROKEN OR SHOWS ANY SIGNS OF TAMPERING

*This product is not manufactured or distributed by Bayer
HealthCare LLC, owner of the registered trademark Coricidin®
HBP Maximum Strength Multi-Symptom Flu.
50844 ORG101973808

Distributed by: CVS Pharmacy, Inc.
One CVS Drive, Woonsocket, RI 02895
© 2025 CVS/pharmacy
CVS.com® 1-800-SHOP CVS

V-19849

100% money back
guaranteed.
CVS.com/returnpolicy

CVS 44-738